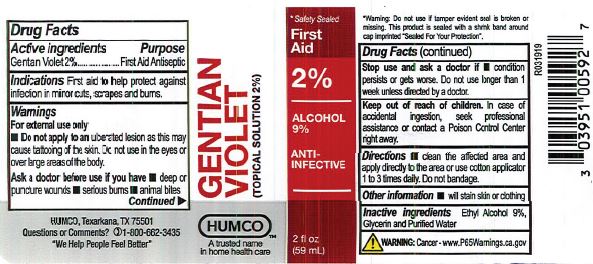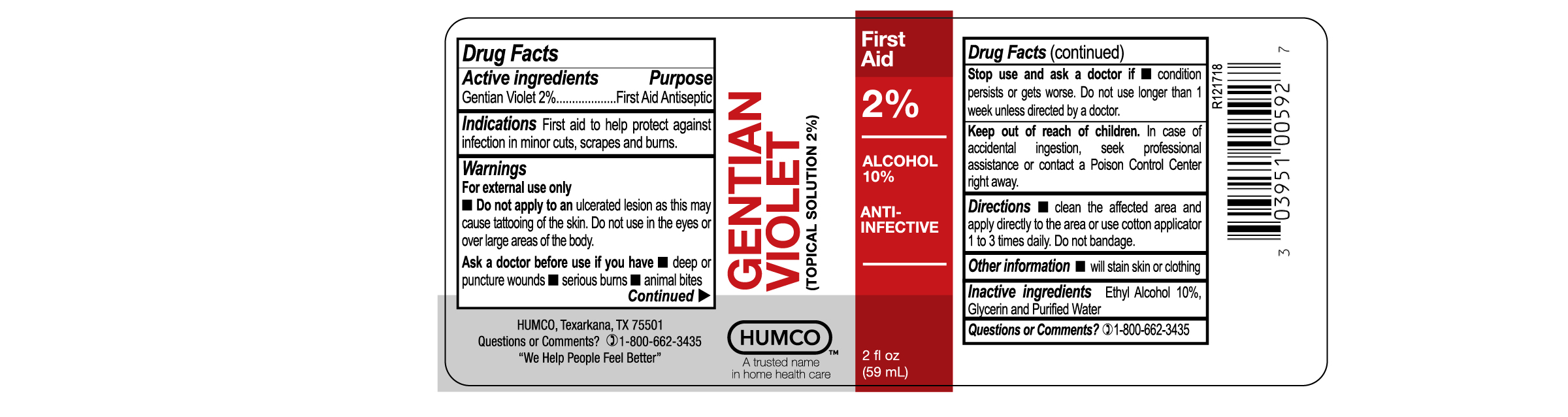 DRUG LABEL: Humco Gentian Violet 2%
NDC: 0395-1005 | Form: LIQUID
Manufacturer: Humco Holding Group, Inc.
Category: otc | Type: HUMAN OTC DRUG LABEL
Date: 20231215

ACTIVE INGREDIENTS: GENTIAN VIOLET 20 mg/1 mL
INACTIVE INGREDIENTS: ALCOHOL; WATER

Humco Gentian Violet 2%

Drug Facts

Active ingredient

Gentian Violet 2%

Purpose

Antiseptic

Uses

For external treatment of abrasions, minor cuts, surface injuries, and superficial infections of the skin.

Warnings

For external use only.

Do not apply to an ulcerative lesion as this may cause tattoing of the skin.

Do not use in the eyes.

Ask a doctor before use if

Redness, irritation, swelling or pain persists or increases of if infection occurs.

Keep out of reach of children.

In case of accidental ingestion, seek professional assistance or contact a Poison Control Center right away.

Directions

Clean the affected area and apply directly to the wound or use cotton applicator once or twice daily. Do not bandage.

Other information

Will stain skin or clothing.

Inactive ingredients

Alcohol and Purified water

Questions or Comments?

1-800-662-3435